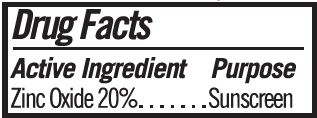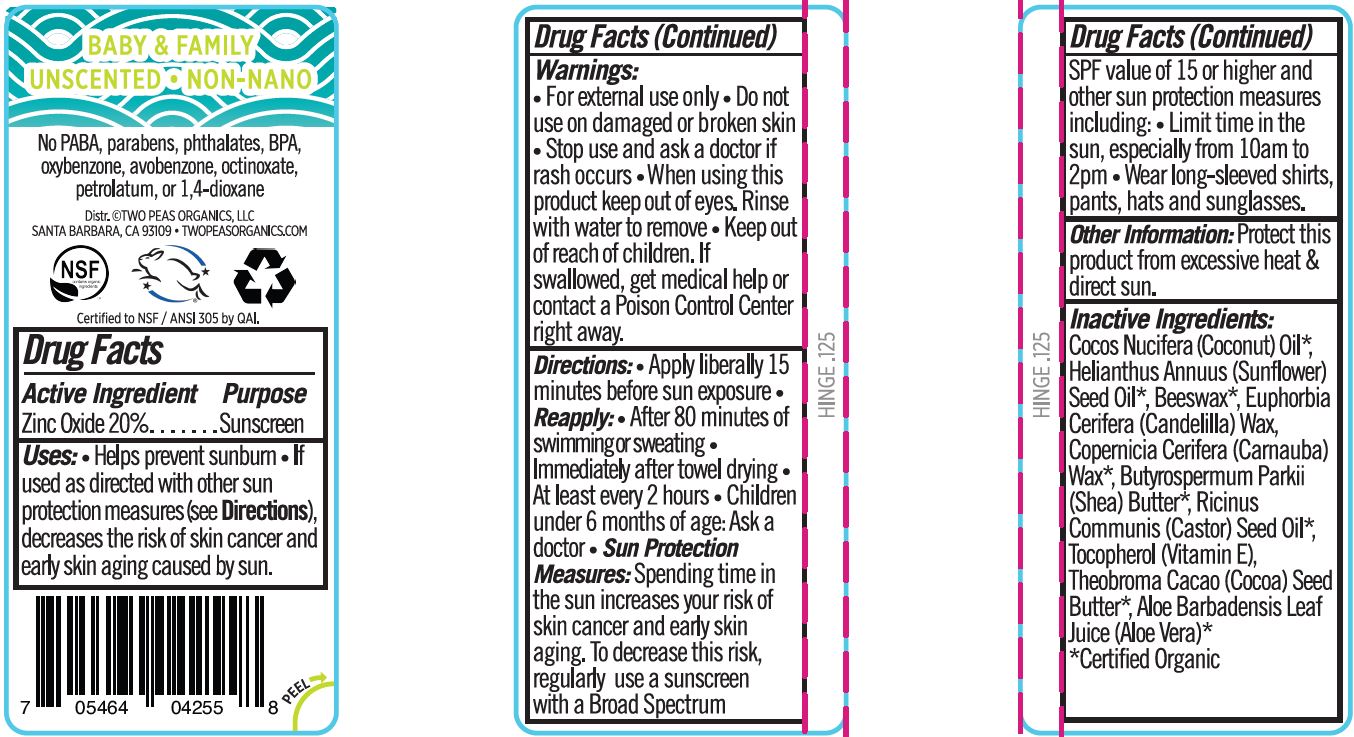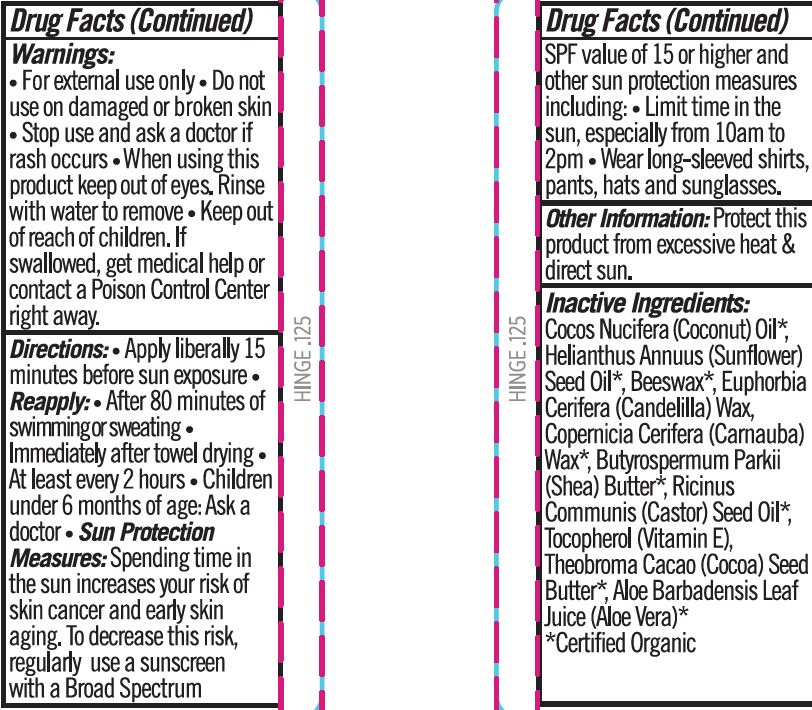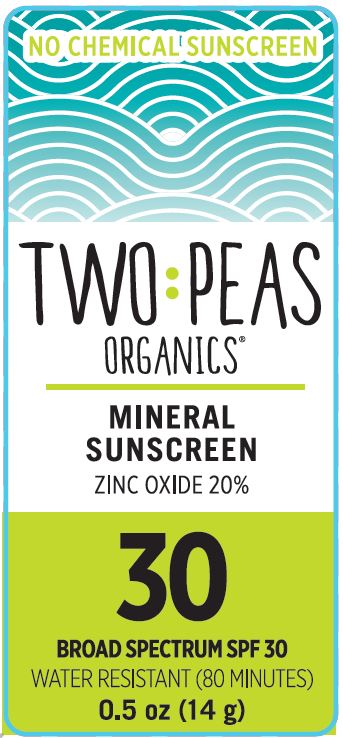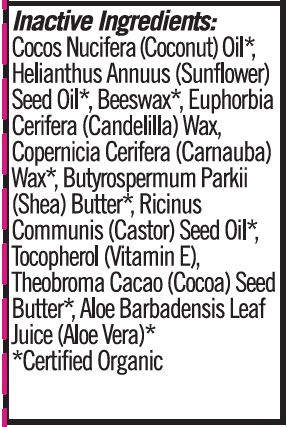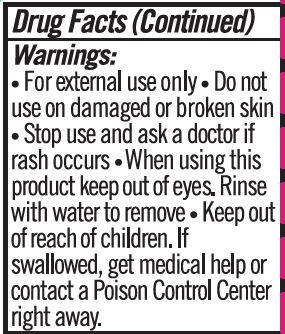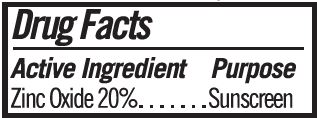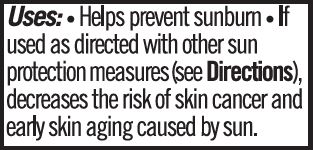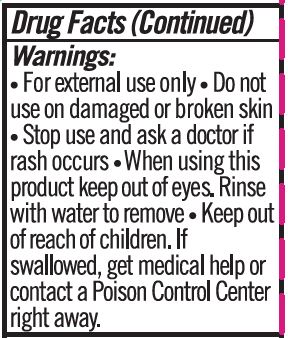 DRUG LABEL: Sunscreen
NDC: 62932-254 | Form: STICK
Manufacturer: Private Label Select Ltd CO
Category: otc | Type: HUMAN OTC DRUG LABEL
Date: 20211229

ACTIVE INGREDIENTS: ZINC OXIDE 20 g/100 g
INACTIVE INGREDIENTS: .BETA.-TOCOPHEROL; CARNAUBA WAX; COCOA BUTTER; .DELTA.-TOCOPHEROL; ALOE VERA LEAF; SUNFLOWER OIL; SHEA BUTTER; WHITE WAX; .GAMMA.-TOCOPHEROL; CANDELILLA WAX; .ALPHA.-TOCOPHEROL, D-; CASTOR OIL; COCONUT OIL

Two Peas, Mineral SPF 30 Sunstick